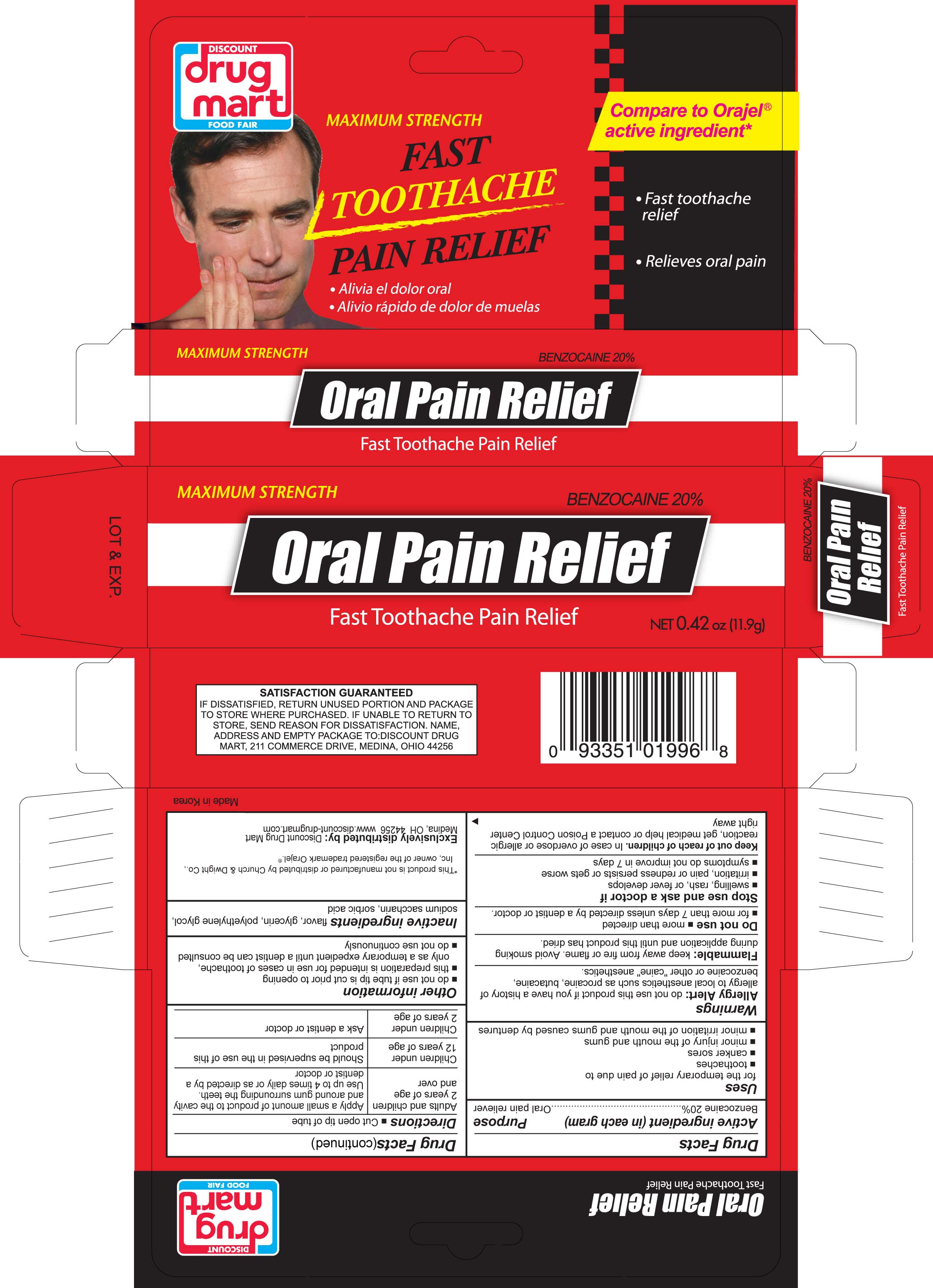 DRUG LABEL: Oral Pain Relief
NDC: 53943-996 | Form: GEL
Manufacturer: Discount Drug Mart, Inc.
Category: otc | Type: HUMAN OTC DRUG LABEL
Date: 20171227

ACTIVE INGREDIENTS: BENZOCAINE 200 mg/1 g
INACTIVE INGREDIENTS: POLYETHYLENE GLYCOL; SACCHARIN SODIUM; SORBIC ACID; GLYCERIN

Drug Facts

Active ingredient (in each gram)

Benzocaine 20%

Purpose

Oral Pain Reliever

Uses

for the temporary relief of pain due to

- toothaches
- canker sores
- minor injury of the mouth and gums
- minor irritation of the mouth and gums caused by dentures

Warnings

Allergy alert: do not use this product if you have a history of allergy to local anesthetics such as procaine, butacaine, benzocaine or other "caine" anesthetics

WARNINGS

Flammable: keep away from fire or flame. Avoid smoking during application and until this product has dried.

Do not use

more than directed for more than 7 days unless told to do so by a dentist or doctor

Stop use and ask a doctor if

swelling, rash or fever develops; irritation, pain or redness persists or worsens; symptoms do not improve in 7 days

Keep out of reach of children. In case of overdose or allergic reaction, get medical help or contact a Poison Control Center right away.

Directions

Directions cut open tip of tube

Adults and children 2 years of age and over | Apply a small amount of product to the cavity and around gum surrounding the teeth. Use up to 4 times daily or as directed by a dentist or doctor
Children under 12 years of age | Should be supervised in the use of this product
Children under 2 years of age | Ask a dentist or doctor

Inactive ingredients

Inactive ingredients flavor, glycerin, polyethylene glycol, sodium saccharin, sorbic acid,

Other Information

- do not use if tube tip is cut prior to opening
- this preparation is intended for use in case of toothache, only as a temporary expedient until a dentist can be consulted
- do not use continuously

PACKAGE LABEL

Discount Drug Mart Oral Pain Relief